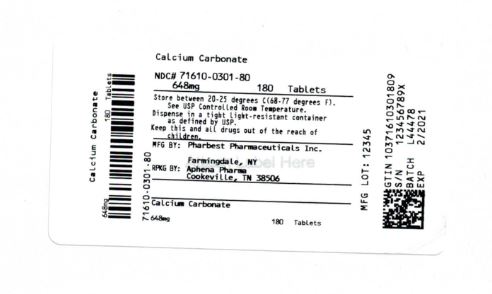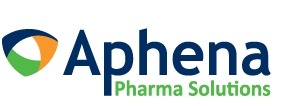 DRUG LABEL: Calcium Carbonate 10 gr (648 mg)
NDC: 71610-301 | Form: TABLET
Manufacturer: Aphena Pharma Solutions - Tennessee, LLC
Category: otc | Type: HUMAN OTC DRUG LABEL
Date: 20250109

ACTIVE INGREDIENTS: CALCIUM CARBONATE 648 mg/1 1
INACTIVE INGREDIENTS: ACACIA; CROSCARMELLOSE SODIUM; MAGNESIUM STEARATE; MALTODEXTRIN; MICROCRYSTALLINE CELLULOSE; STEARIC ACID

Drug Facts

Active ingredient (in each tablet)

Calcium Carbonate 10 gr (648 mg)

Purpose

Antacid

Uses

relieves

- acid indigestion
- heartburn
- sour stomach
- upset stomach associated with these symptoms

Warnings

Ask a doctor before use if you have

- kidney stones
- a calcium-restricted diet

Ask a doctor or pharmacist before use if you are

taking a prescription drug. Antacids may interact with certain prescription drugs.

Stop use and ask a doctor if

symptoms last more than 2 weeks.

If pregnant or breast-feeding,

ask a health professional before use.

Directions

- take one to four tablets daily
- do not take more than 4 tablets in 24 hours
- do not use the maximum dosage for more than two weeks

Other information

- each tablet contains: calcium 260 mg
- store at room temperature

Inactive ingredients

acacia, croscarmellose sodium, magnesium stearate, maltodextrin, microcrystalline cellulose, stearic acid

Questions or comments?

1-800-645-2158

TAMPER EVIDENT: DO NOT USE IF IMPRINTED SEAL UNDER CAP IS BROKEN OR MISSING

This is a bulk package. Dispense contents with a child-resistant closure in a tight, light-resistant container as defined in the USP.

Repackaging Information

Please reference the How Suppliedsection listed above for a description of individual tablets. This drug product has been received by Aphena Pharma - TN in a manufacturer or distributor packaged configuration and repackaged in full compliance with all applicable cGMP regulations. The package configurations available from Aphena are listed below:

Count | 648 mg
180 | 71610-301-80

Store between 20°-25°C (68°-77°F). See USP Controlled Room Temperature. Dispense in a tight light-resistant container as defined by USP. Keep this and all drugs out of the reach of children.

Repackaged by:
Cookeville, TN 38506
20190711JH

PRINCIPAL DISPLAY PANEL - 648 mg

NDC 71610-301 - Calcium Carbonate 648 mg Tablets